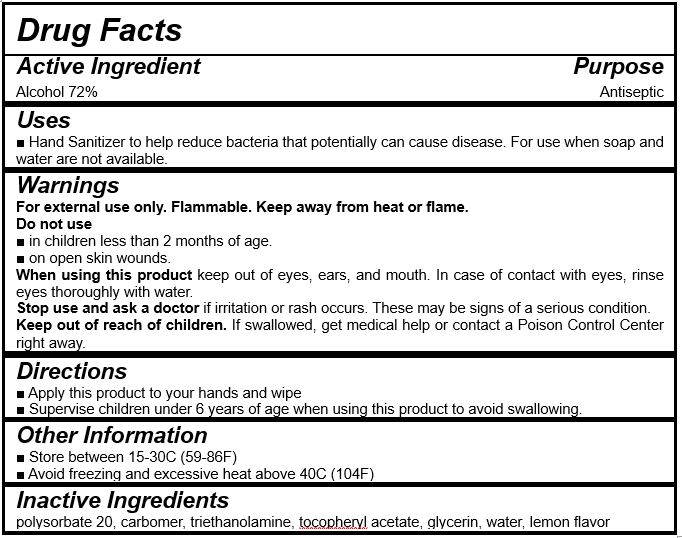 DRUG LABEL: Wonder Hand Gel (ethanol) 72% 30ml
NDC: 74279-0013 | Form: GEL
Manufacturer: Dai Kyoung Pharmaceutic Co.,Ltd.
Category: otc | Type: HUMAN OTC DRUG LABEL
Date: 20201120

ACTIVE INGREDIENTS: ALCOHOL 21.6 mL/30 mL
INACTIVE INGREDIENTS: WATER; POLYSORBATE 20; CARBOMER HOMOPOLYMER, UNSPECIFIED TYPE; TROLAMINE; GLYCERIN

PLUS / Dai Kyoung Pharmaceutic Co.,Ltd. - Wonder Hand Gel (ethanol) 72% 30ml

ACTIVE INGREDIENT

Alcohol (Ethanol)

INACTIVE INGREDIENT

Polysorbate 20, Carbomer, Triethanolamine, Tocopheryl Acetate, Glycerin, Water, Lemon Flavor

PURPOSE

Hand sanitizer to help reduce bacteria that potentially can cause disease. For use when soap and water are not available.

keep out of reach of the children

INDICATIONS AND USAGE

Place enough product on hands to cover all surfaces. Rub hands together until dry.

Supervise children under 6 years of age when using this product to avoid swallowing.

WARNINGS

For external use only. Flammable. Keep away from heat or flame.

Do not use

- in children less than 2 months of age
- on open skin wounds

When using this product keep out of eyes, ears, and mouth. In case of contact with eyes, rinse thoroughly with water.

Stop use and ask a doctor if irritation or rash occurs. These may be signs of a serious condition.

Keep out of reach of children. If swallowed, get medical help or contact a Poison Control Center right away.

DOSAGE AND ADMINISTRATION

for external use only